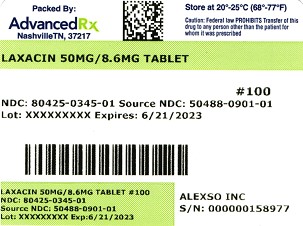 DRUG LABEL: Laxacin
NDC: 80425-0345 | Form: TABLET
Manufacturer: Advanced Rx Pharmacy of Tennessee, LLC
Category: otc | Type: HUMAN OTC DRUG LABEL
Date: 20241231

ACTIVE INGREDIENTS: DOCUSATE SODIUM 50 mg/1 1; SENNOSIDES A AND B 8.6 mg/1 1
INACTIVE INGREDIENTS: CROSCARMELLOSE SODIUM; D&C YELLOW NO. 10; DEXTROSE, UNSPECIFIED FORM; ANHYDROUS DIBASIC CALCIUM PHOSPHATE; FD&C YELLOW NO. 6; HYPROMELLOSE, UNSPECIFIED; MAGNESIUM STEARATE; MICROCRYSTALLINE CELLULOSE; POLYETHYLENE GLYCOL, UNSPECIFIED; SODIUM BENZOATE; STEARIC ACID; TITANIUM DIOXIDE; SILICON DIOXIDE

Laxacin Tablets

DO NOT USE IF IMPRINTED SAFETY SEAL UNDER CAP IS BROKEN OR MISSING

Drug Facts

Active ingredients (in each tablet)

Docusate Sodium 50 mg

Sennosides 8.6 mg

Purposes

Stool softener

Laxative

Uses

- relieves occasional constipation (irregularity)
- generally produces a bowel movement in 6-12 hours

Warnings

Do not use

- if you are now taking mineral oil, unless directed by a doctor
- laxative products for longer than 1 week unless directed by a doctor

Ask a doctor before use if you have

- stomach pain
- nausea
- vomiting
- noticed a sudden change in bowel habits that continues over a period of 2 weeks

Stop use and ask a doctor ifyou have rectal bleeding or fail to have a bowel movement after use of a laxative. These may indicate a serious condition.

PREGNANCY OR BREAST FEEDING

If pregnant or breast-feeding,ask a health professional before use.

Keep out of reach of children.In case of overdose, get medical help or contact a Poison Control Center right away.

Directions

- take preferably at bedtime or as directed by a doctor

age | starting dose | maximum dose
adults and children 12; years and older | 2 tablets once a day | 4 tablets twice a day
children 6 to under 12 years | 1 tablet once a day | 2 tablets twice a day
children 2 to under 6 years | 1/2 tablet once a day | 1 tablet twice a day
children under 2 years | ask a doctor | ask a doctor

Other information

- each tablet contains: calcium 20 mg, sodium 4 mg
- keep lid tightly closed
- store at room temperature in a dry place

INACTIVE INGREDIENT

Inactive ingredientsCroscarmellose sodium, D&C yellow #10, dextrose, dicalcium phosphate, FD&C yellow #6, hypromellose, magnesium stearate, microcrystalline cellulose, polyethylene glycol, silica, sodium benzoate, stearic acid, titanium dioxide.

QUESTIONS

Questions?If you have any questions or comments, or to report an adverse event, please contact (800) 495-6078

Laxacin tablets are supplied as follows:

Bottles of 100 tablets NDC: 80425-0345-01

Manufactured for:

Alexso Inc.

Los Angeles, CA 90064

Distributed by:

Advanced Rx Pharmacy of Tennessee, LLC